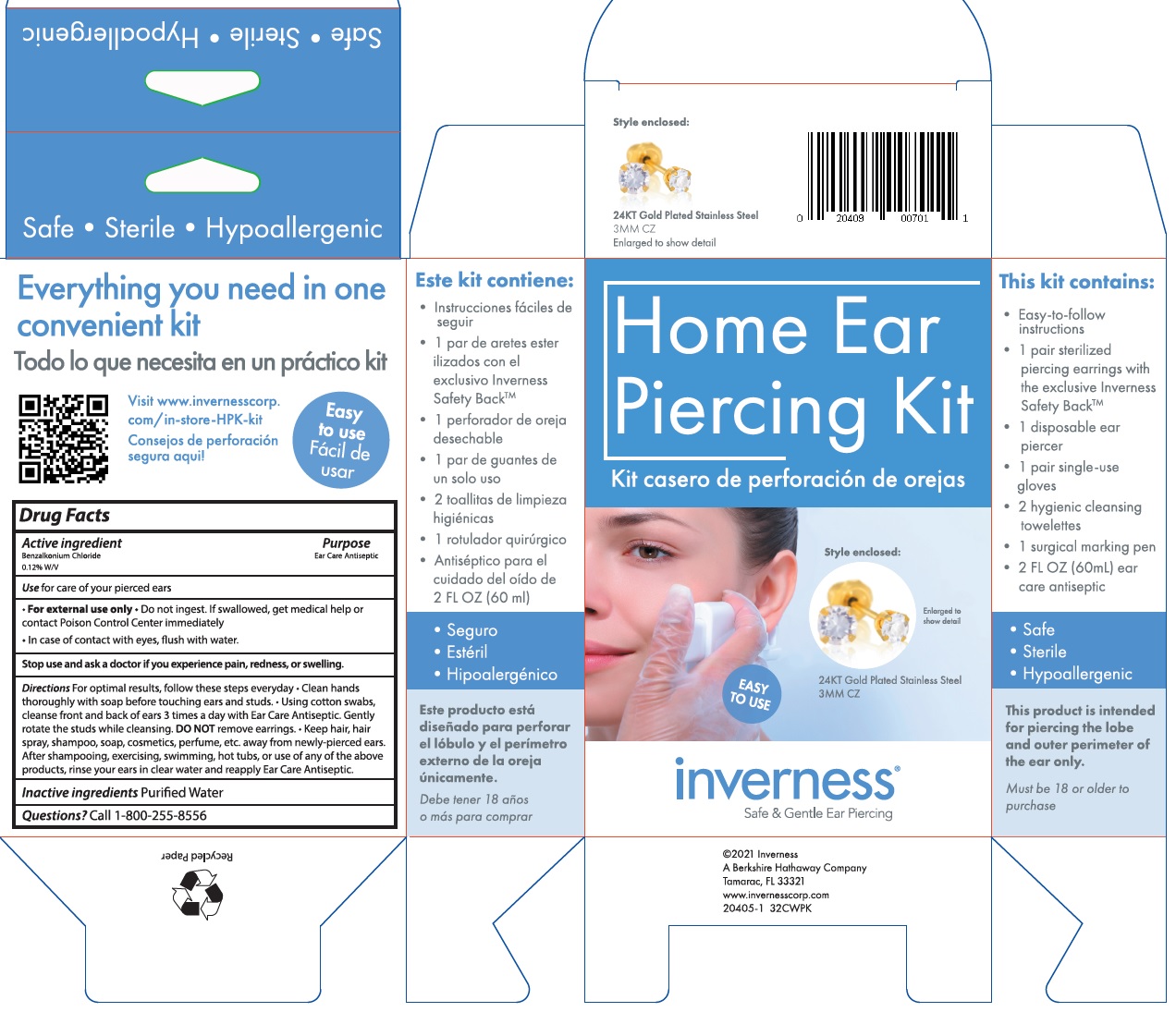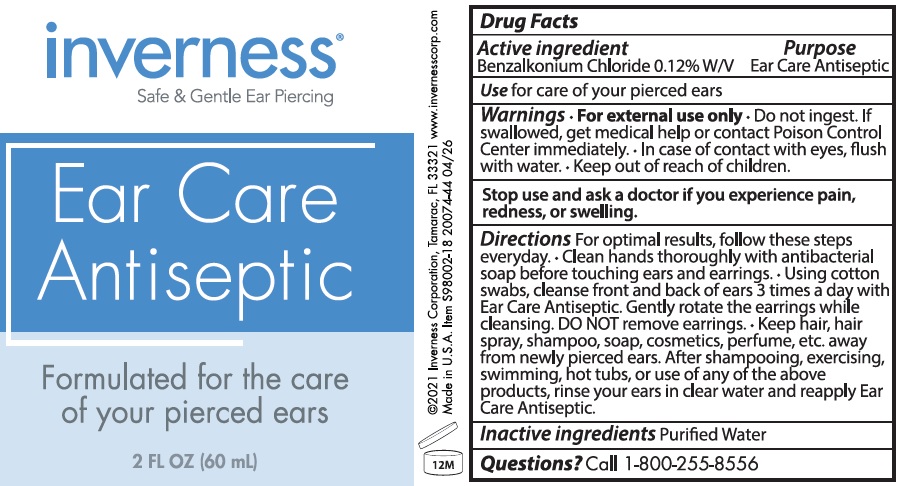 DRUG LABEL: Inverness Home Ear Piercing Kit
NDC: 70094-004 | Form: KIT | Route: TOPICAL
Manufacturer: The Richline Group, Inc.
Category: otc | Type: HUMAN OTC DRUG LABEL
Date: 20250217

ACTIVE INGREDIENTS: BENZALKONIUM CHLORIDE 1.2 mg/1 mL
INACTIVE INGREDIENTS: WATER

Inverness Home Ear Piercing Kit

Active ingredient

Benzalkonium Chloride 0.12% W/V

Purpose

Ear Care Antiseptic

Use

for care of your pierced ears

WARNINGS

- For external use only
- Do not ingest. If swallowed, get medical help or contact Poison Control Center immediately
- In case of contact with eyes, flush with water.

Stop use and ask a doctor if

you experience pain, redness, or swelling.

Directions

For optimal results, follow these steps everyday • Clean hands thoroughly with soap before touching ears and studs. • Using cotton swabs, cleanse front and back of ears 3 times a day with Ear Care Antiseptic. Gently rotate the studs while cleansing. DO NOT remove earrings. • Keep hair, hair spray, shampoo, soap, cosmetics, perfume, hot tubs, or use of any of the above products, rinse your ears in clear water and reapply Ear Care Antiseptic

Inactive ingredients

Purified Water

Questions?

Call 1-800-255-8556

Active ingredient

Benzalkonium Chloride 0.12% W/V

Purpose

Ear Care Antiseptic

Use

for care of your pierced ears

Warnings

- For external use only
- Do not ingest. If swallowed, get medical help or contact Poison Control Center immediately
- In case of contact with eyes, flush with water.

Stop use and ask a doctor if

you experience pain, redness, or swelling.

Directions

For optimal results, follow these steps everyday. • Clean hands thoroughly with antibacterial soap before touching ears and earrings. • Using cotton swabs, cleanse front and back of ears 3 times a day with Ear Care Antiseptic. Gently rotate the earrings while cleansing. DO NOT remove earrings. • Keep hair, hair spray, shampoo, soap, cosmetics, perfume, etc. away from newly pierced ears. After shampooing, exercising, swimming, hot tubs, or use of any of the above products, rinse your ears in clear water and reapply Ear Care Antiseptic.

Inactive ingredients

Purified Water

Questions?

Call 1-800-255-8556